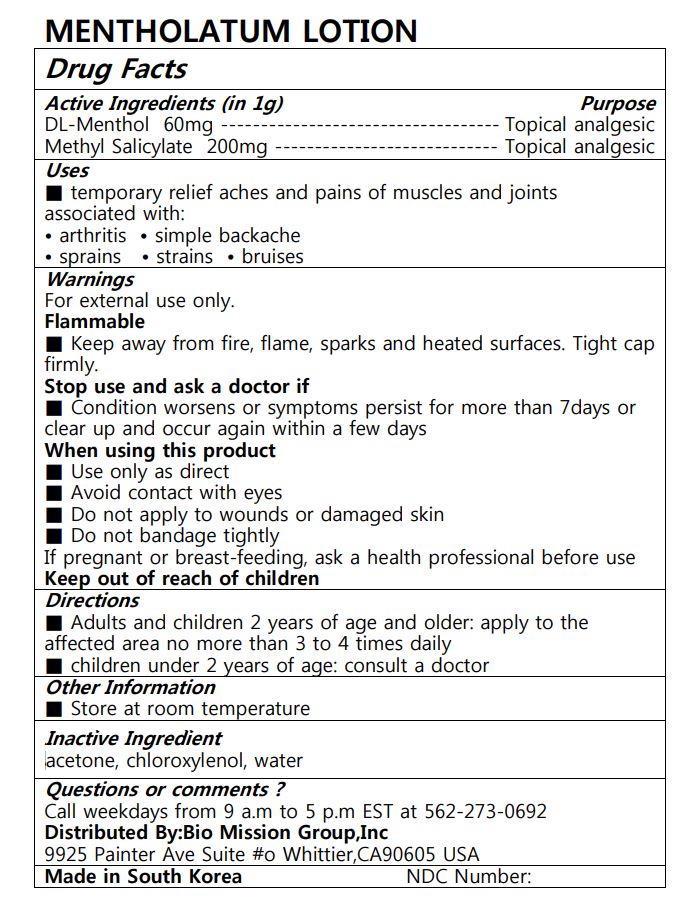 DRUG LABEL: Mentholatum
NDC: 72988-0031 | Form: LOTION
Manufacturer: Lydia Co., Ltd.
Category: otc | Type: HUMAN OTC DRUG LABEL
Date: 20230706

ACTIVE INGREDIENTS: METHYL SALICYLATE 200 mg/1 g; MENTHOL 60 mg/1 g
INACTIVE INGREDIENTS: MINERAL OIL; WATER

ACTIVE INGREDIENT

Methyl Salicylate, DL-Menthol

PURPOSE

temporary relief aches and pains of muscles and joints associated with: • arthritis • simple backache • sprains • strains • bruises

Keep out of reach of children

INDICATIONS AND USAGE

■ Adults and children 2 years of age and older: apply to the affected area no more than 3 to 4 times daily ■ children under 2 years of age: consult a doctor

WARNINGS

Warnings For external use only. Flammable ■ Keep away from fire, flame, sparks and heated surfaces. Tight cap firmly. Stop use and ask a doctor if ■ Condition worsens or symptoms persist for more than 7days or clear up and occur again within a few days When using this product ■ Use only as direct ■ Avoid contact with eyes ■ Do not apply to wounds or damaged skin ■ Do not bandage tightly If pregnant or breast-feeding, ask a health professional before use Keep out of reach of childre

INACTIVE INGREDIENT

mineral oil, lantrol, Sorbitan Monostearate, etc

DOSAGE AND ADMINISTRATION

topocal use